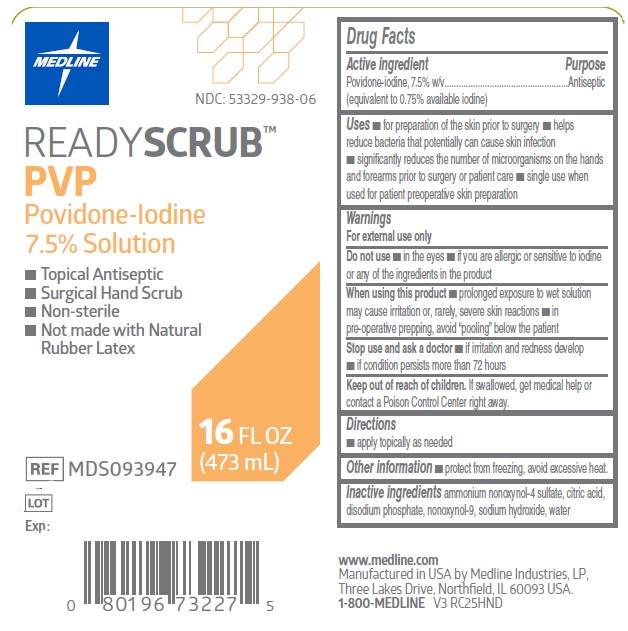 DRUG LABEL: Povidone-Iodine
NDC: 53329-938 | Form: SOLUTION
Manufacturer: Medline Industries, LP
Category: otc | Type: HUMAN OTC DRUG LABEL
Date: 20251022

ACTIVE INGREDIENTS: POVIDONE-IODINE 0.75 g/100 mL
INACTIVE INGREDIENTS: AMMONIUM NONOXYNOL-4 SULFATE; NONOXYNOL-5; CITRIC ACID MONOHYDRATE; SODIUM PHOSPHATE, DIBASIC, DIHYDRATE; SODIUM HYDROXIDE; WATER

938 ReadyScrub PVP

Active ingredient

Povidone-Iodine 7.5% w/v
(equivalent to 0.75% available iodine)

Purpose

Antiseptic

Uses

- for preparation of the skin prior to surgery
- helps to reduce bacteria that potentially can cause skin infection
- significantly reduces the number of microorganisms on the hands and forearms prior to surgery or patient care
- single use when used for patient preoperative skin preparation

Warnings

For external use only

Do not use

- in the eyes
- if you are allergic to iodine or any of the other ingredients in the product

When using this product

- prolonged exposure to wet solution may cause irritation or, rarely, severe skin reactions
- in pre-operative prepping, avoid “pooling” beneath the patient

Stop use and ask a doctor

- if irritation and redness develop
- if condition persists for more than 72 hours

Keep out of reach of children.

If swallowed, get medical help or contact a Poison control center right away.

Directions

- apply topically as needed

Other information

- protect from freezing, avoid excessive heat

Inactive ingredients

ammonium nonoxynol-4 sulfate, citric acid, disodium phosphate, nonoxynol-9, sodium hydroxide, water

Manufactuing Information

www.medline.com

Manufactured in USA by Medline Industries, LP,

Three Lakes Drive, Northfield, IL 60093 USA.

1-800-MEDLINE

REF: MDS093947

Major Change

Update to Directions to remove "follow with application of Medline Prep Solution and allow to dry".